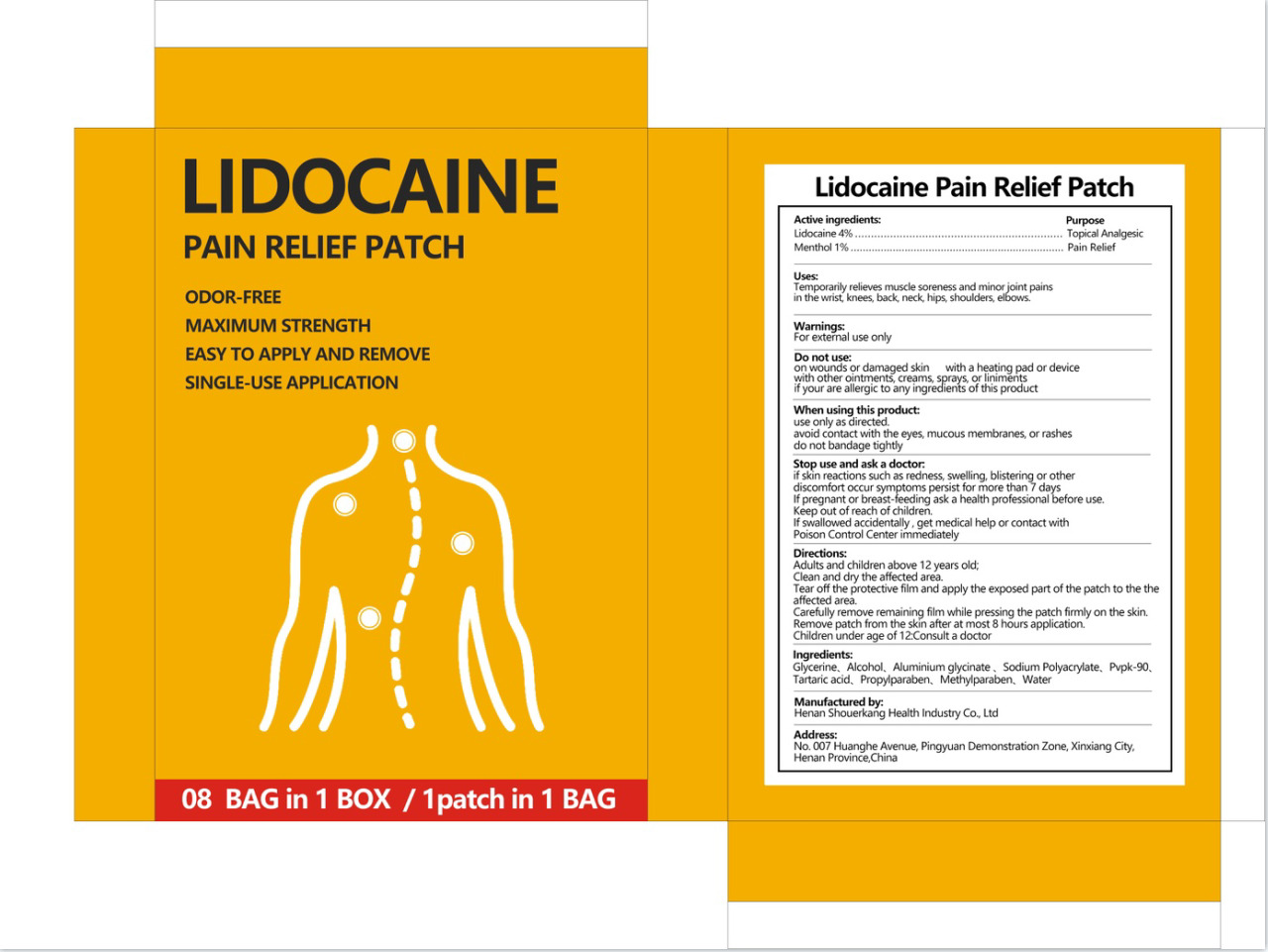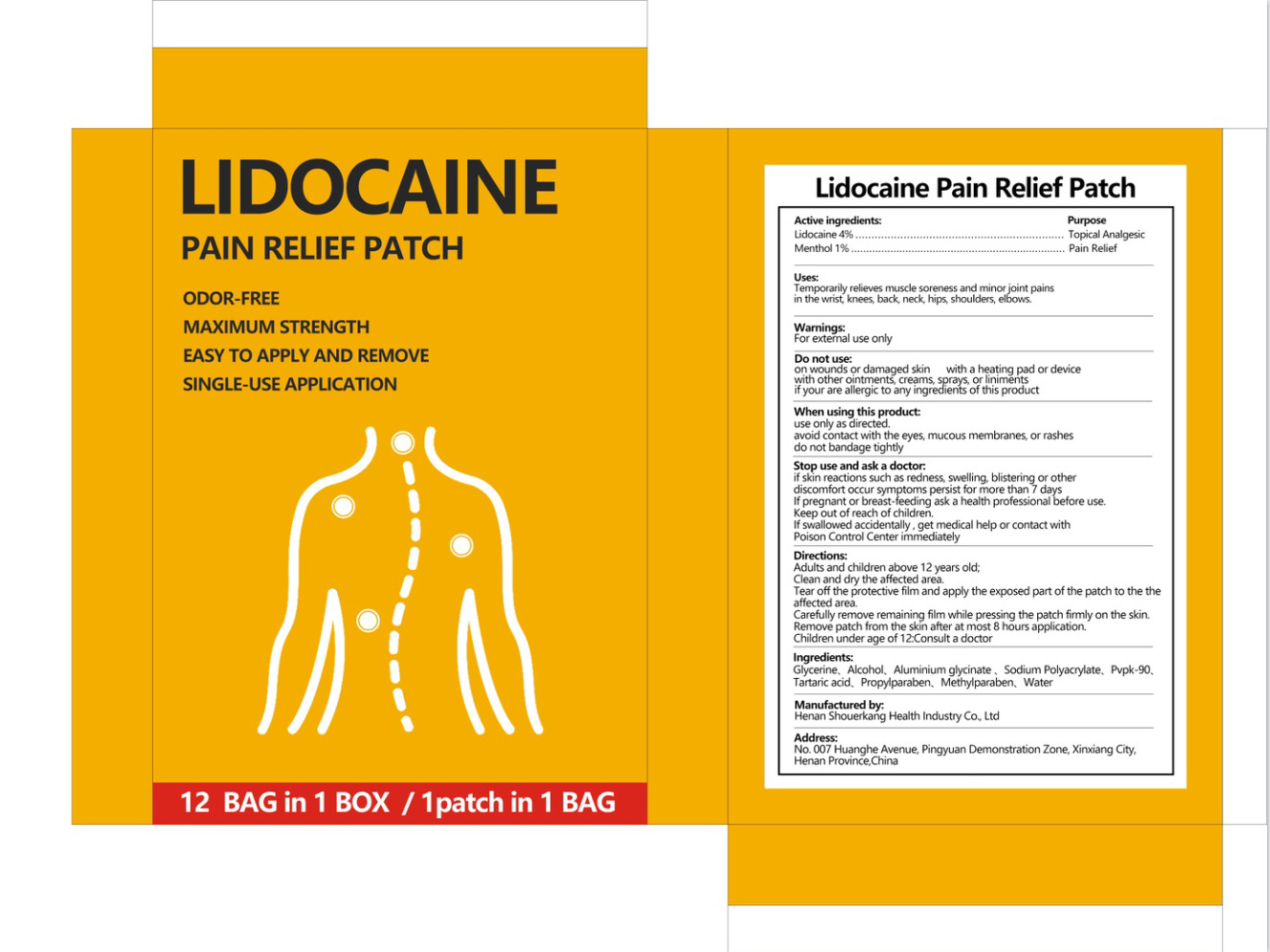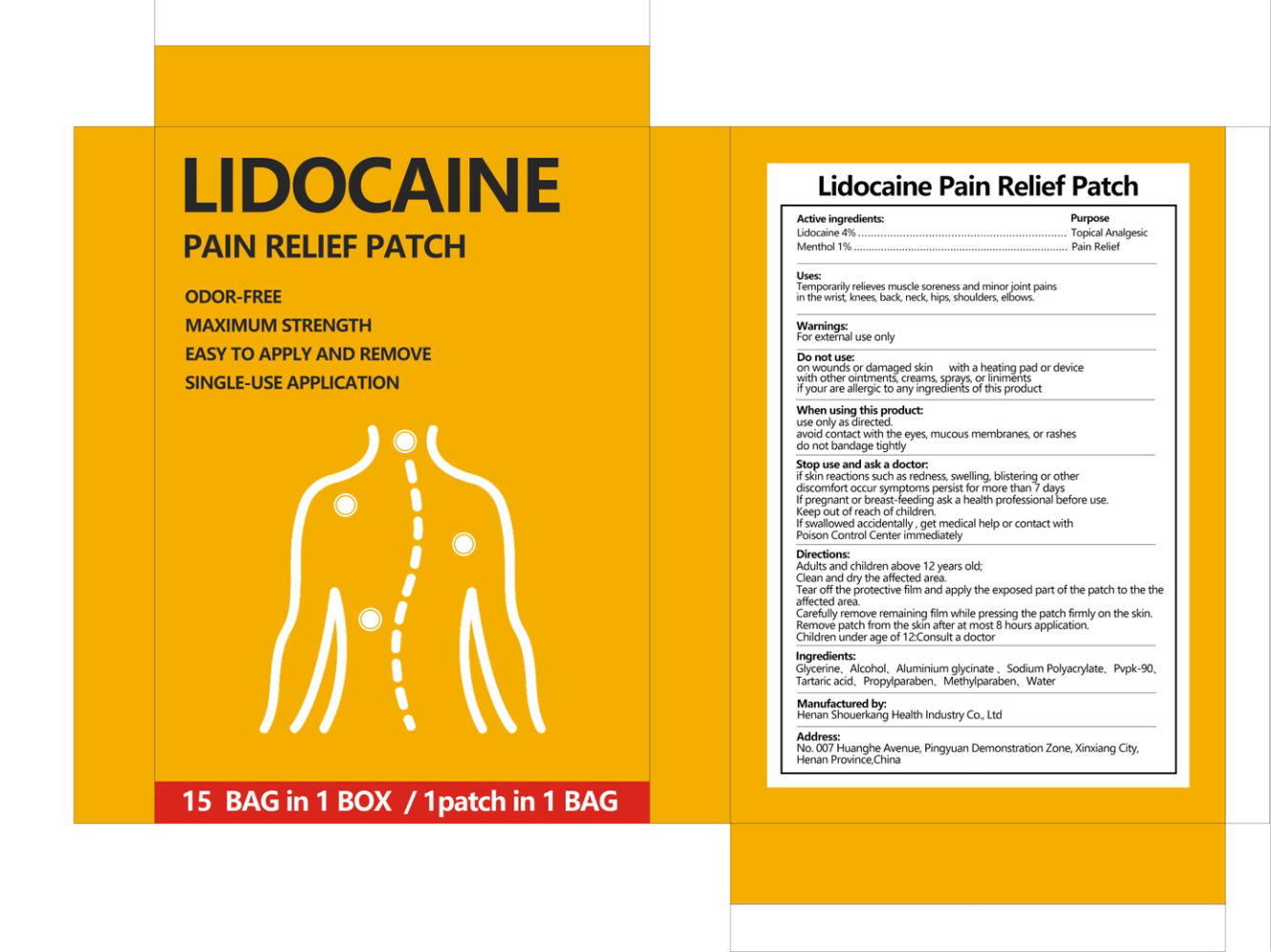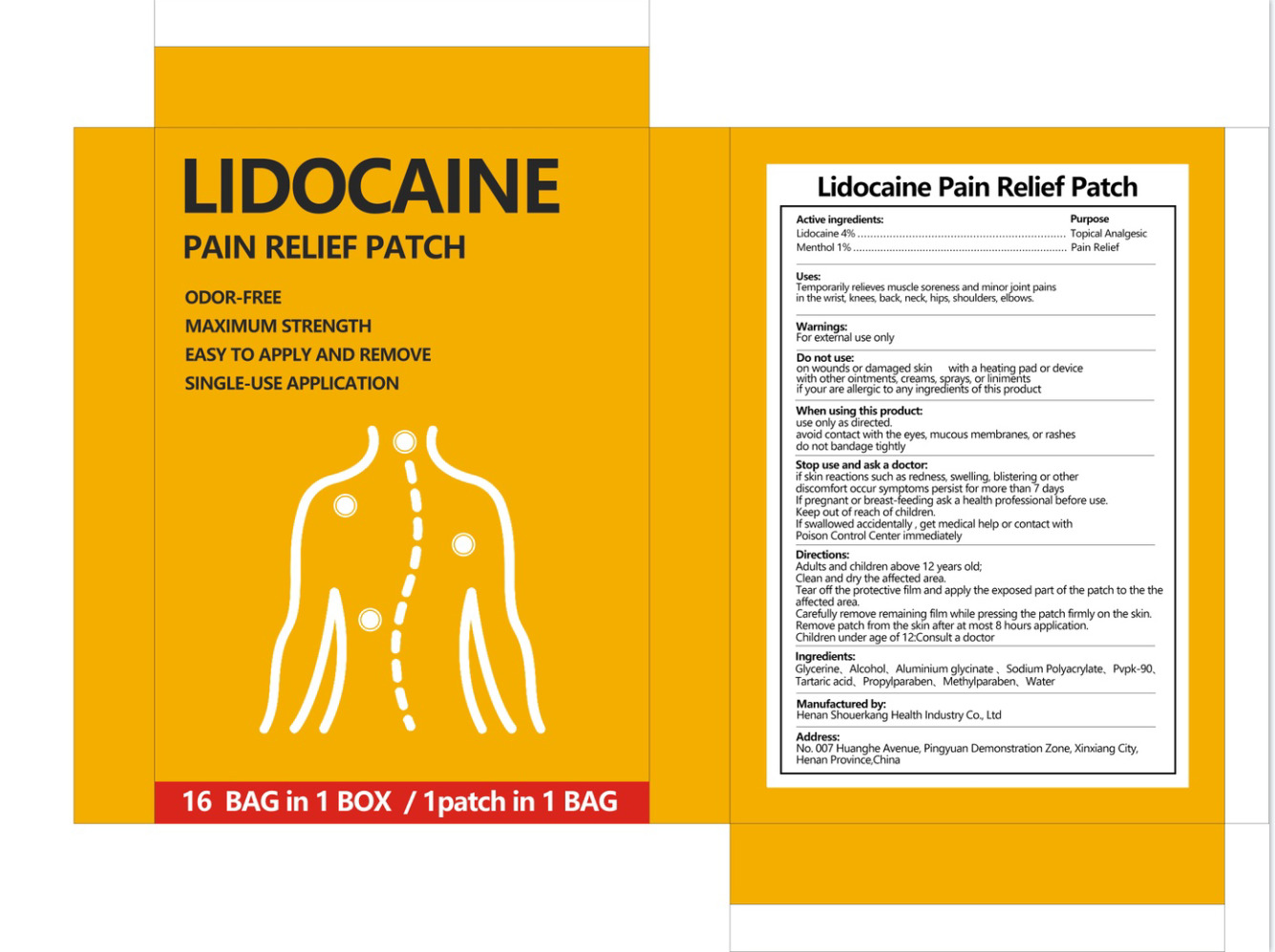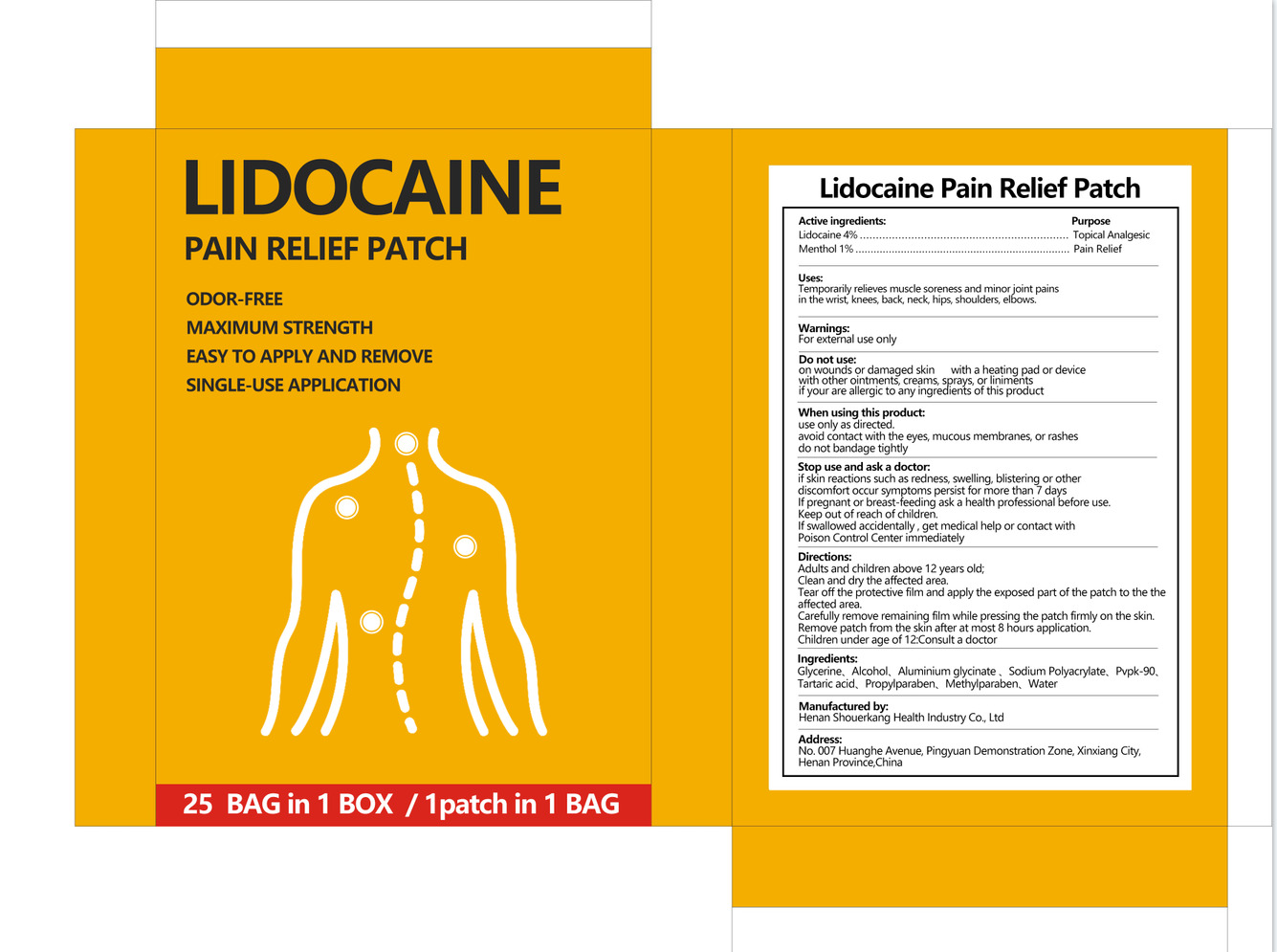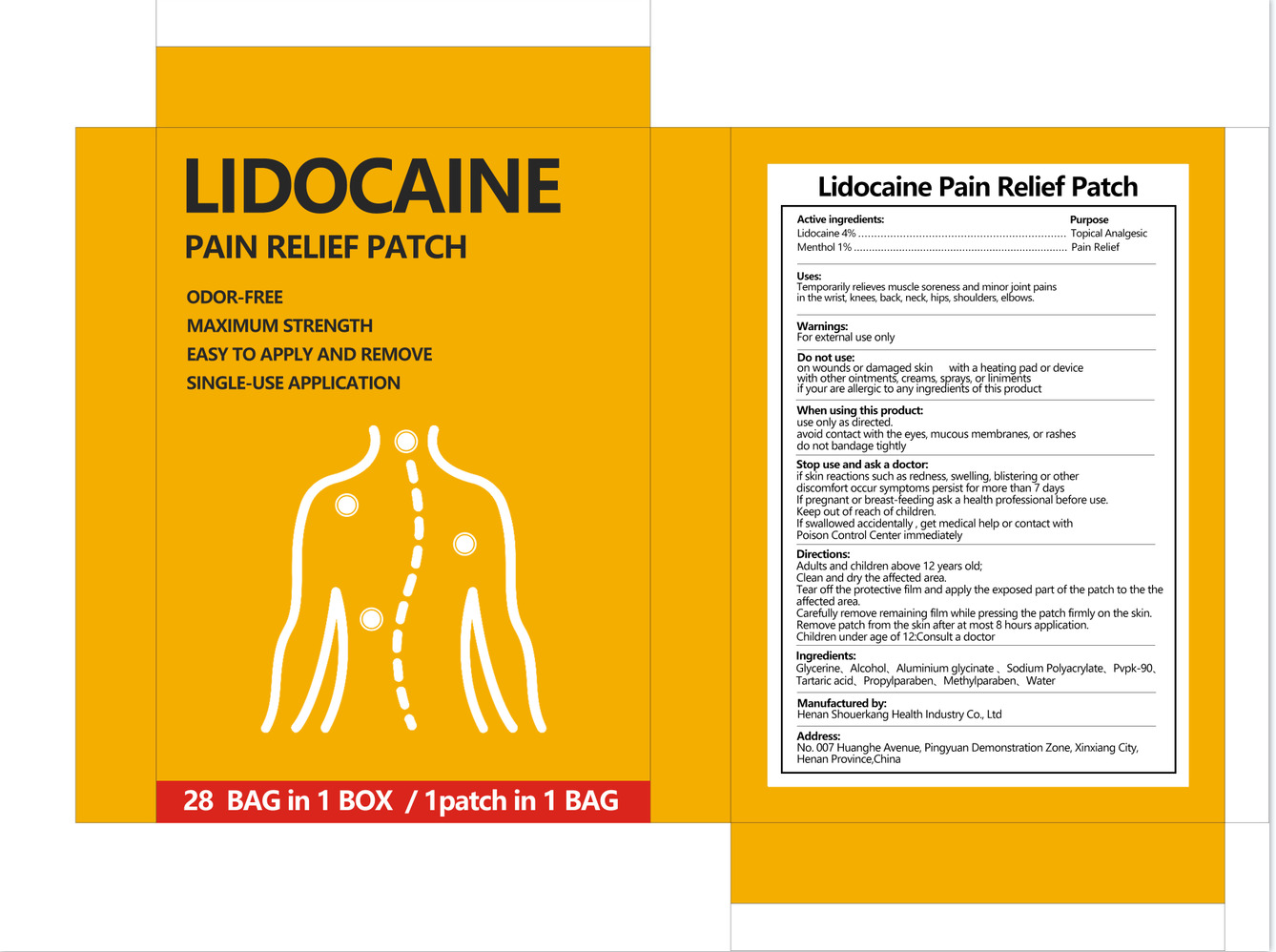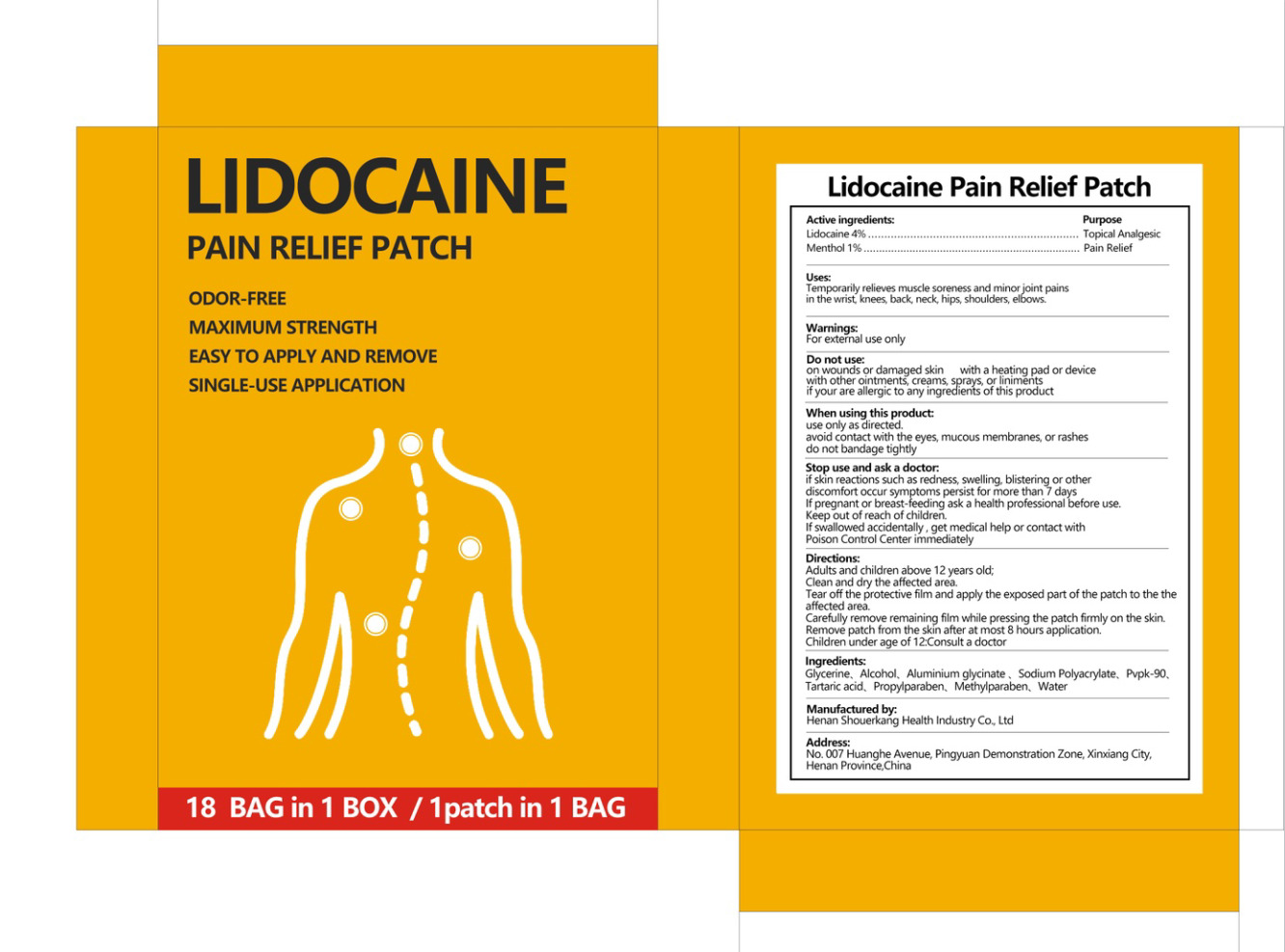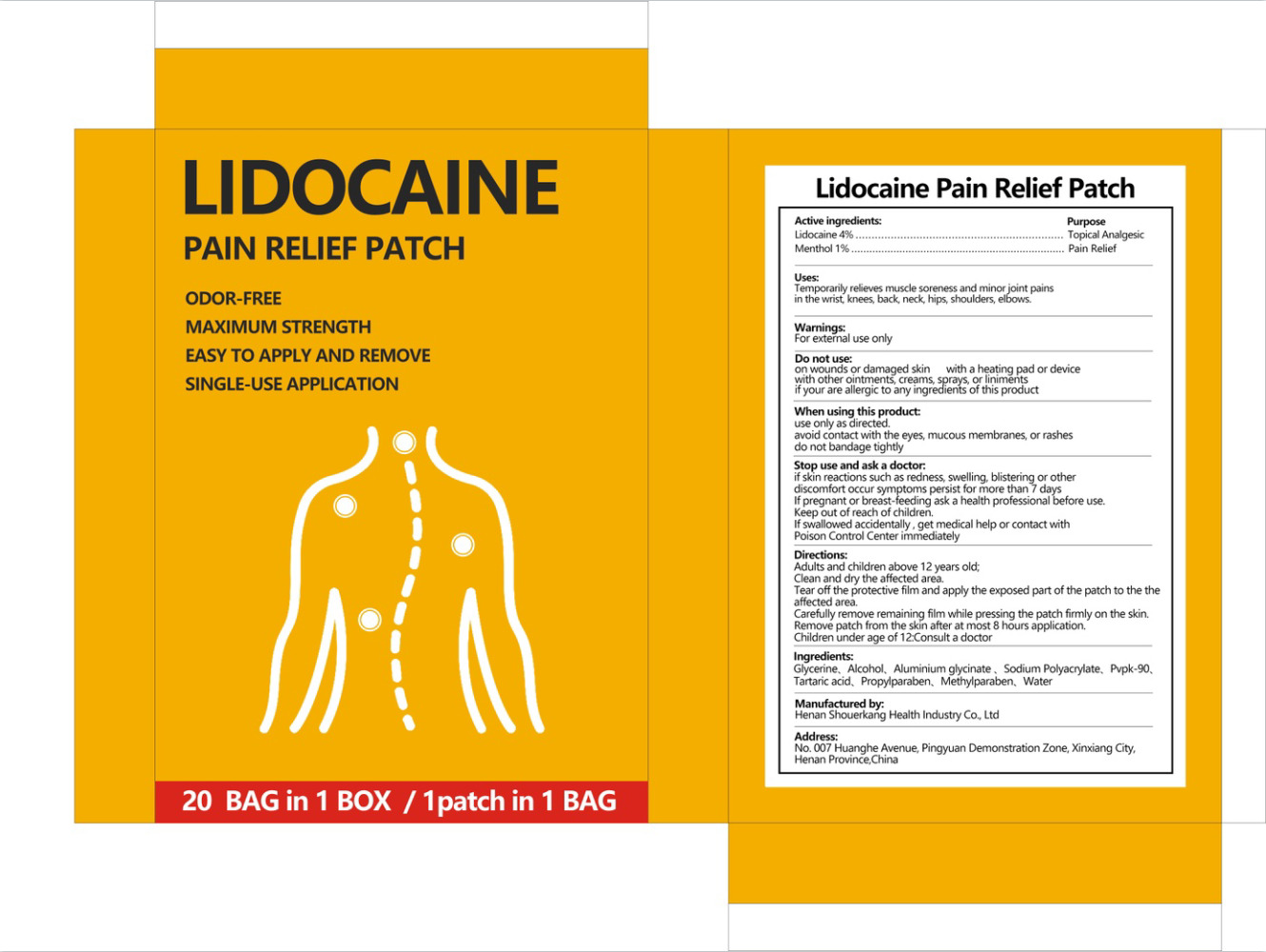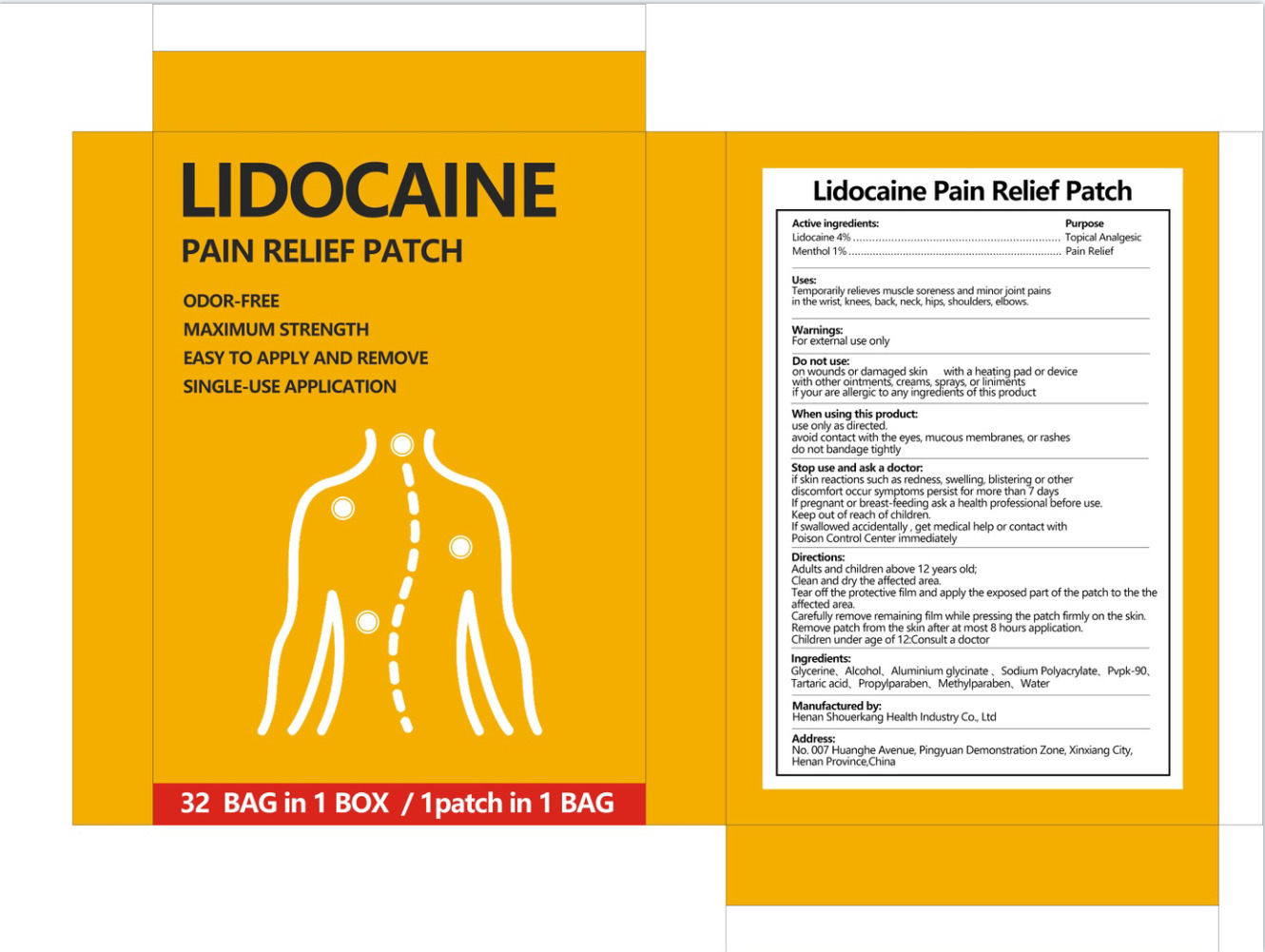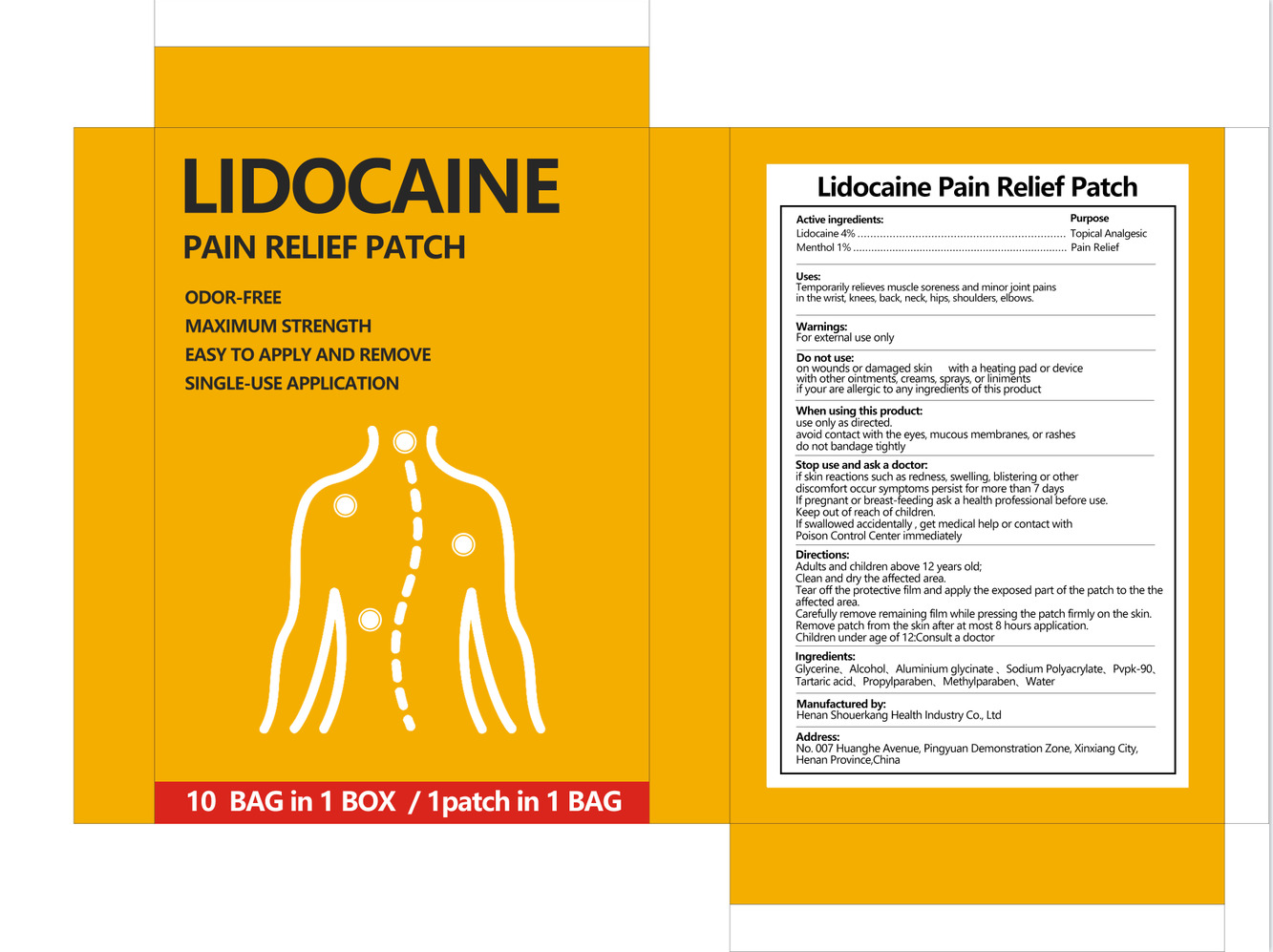 DRUG LABEL: Lidocaine Pain Relief Patch
NDC: 85056-001 | Form: PASTE
Manufacturer: Henan Shouerkang Health Industry Co., Ltd
Category: otc | Type: HUMAN OTC DRUG LABEL
Date: 20260107

ACTIVE INGREDIENTS: MENTHOL 1 g/100 1; LIDOCAINE 4 g/100 1
INACTIVE INGREDIENTS: WATER; PVP; GLYCERIN; SODIUM POLYACRYLATE (8000 MW); DIHYDROXYALUMINUM AMINOACETATE; METHYLPARABEN; PROPYLPARABEN; ALCOHOL; TARTARIC ACID

85056-001

Active Ingredient(s)

Lidocaine 4%

Menthol 1%

Purpose

Topical Analgesic
Pain Relief

Use

Temporarily relieves muscle soreness and minor joint pains
in the wrist, knees, back, neck, hips, shoulders, elbows.

Warnings

For external use only.

Do not use

on wounds or damaged skin with a heating pad or device with other ointments, creams, sprays, or liniments
if your are allergic to any ingredients of this product

WHEN USING

use only as directed. avoid contact with the eyes, mucous membranes, or rashes
do not bandage tightly

STOP USE

if skin reactions such as redness, swelling, blistering or other discomfort occur symptoms persist for more than 7 days
If pregnant or breast-feeding ask a health professional before use. Keep out of reach of children.
If swallowed accidentally , get medical help or contact with Poison Control Center immediately

Keep out of reach of children.

Directions

Adults and children above 12 years old;
Clean and dry the affected area.
Tear off the protective film and apply the exposed part of the patch to the the affected area.
Carefully remove remaining film while pressing the patch firmly on the skin.
Remove patch from the skin after at most 8 hours application.
Children under age of 12:C onsult a doctor

Other information

No Data

Inactive ingredients

Glycerine、Alcohol、 Aluminium glycinate、Sodium Polyacrylate、Pvpk-90、
Tartaric acid Propylparaben、 Methylparaben、 Water